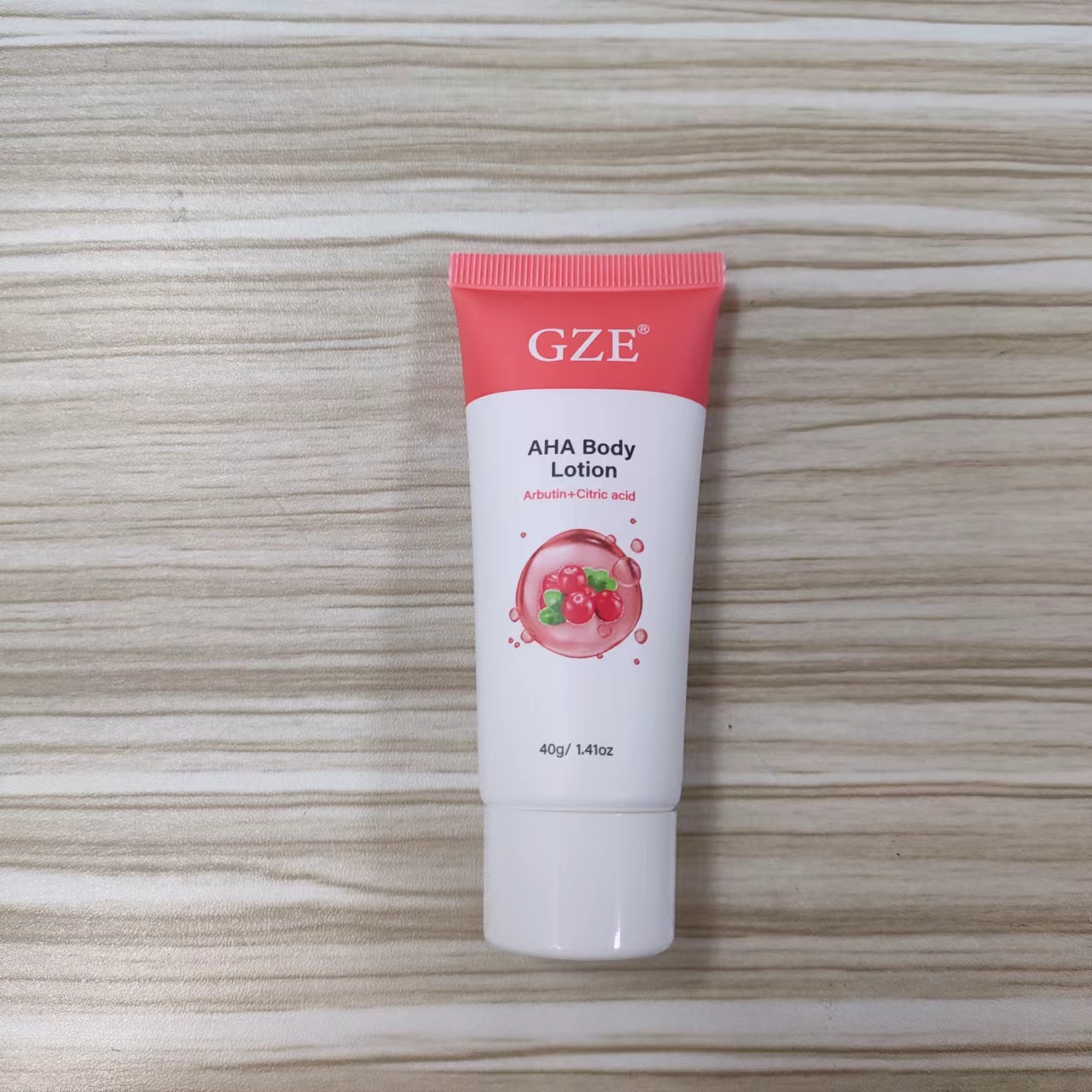 DRUG LABEL: GZE AHA BodyLotion
NDC: 74458-020 | Form: CREAM
Manufacturer: Guangzhou Yilong Cosmetics Co., Ltd
Category: otc | Type: HUMAN OTC DRUG LABEL
Date: 20241128

ACTIVE INGREDIENTS: ARBUTIN 0.4 g/100 g; NIACINAMIDE 0.1 g/100 g; GLUTATHIONE 0.1 g/100 g
INACTIVE INGREDIENTS: BENZOPHENONE-3; CYCLOPENTASILOXANE; SODIUM CHLORIDE; GLYCERIN; PHENOXYETHANOL; TITANIUM DIOXIDE; C12-15 ALKYL BENZOATE; EGG PHOSPHOLIPIDS; BUTYLENE GLYCOL; ETHYLHEXYL METHOXYCINNAMATE; WATER; DIMETHICONE; POLYMETHYLSILSESQUIOXANE; CITRIC ACID MONOHYDRATE; BETAINE; CETYL PEG/PPG-10/1 DIMETHICONE (HLB 2); IMIDAZOLIDINYL UREA; HUMAN TYPE I COLLAGEN

GZE AHA Body Lotion

ACTIVE INGREDIENT

Arbutin 0.4%
Glutathione 0.1%
Niacinamide 0.1%

INACTIVE INGREDIENT

Water

Cyclopentasiloxane

Dimethicone

Glycerin

Diethylhexyl Carbonate

Titanium Dioxide

Butylene Glycol

C12-15 Alkyl Benzoate

Polymethylsilsesquioxane

Citric acid

Polyglyceryl-4Diisostearate/

Polyhydroxystearate/Sebacate

Ethylhexyl Methoxycinnamate

Cetyl PEG/PPG-10/1 Dimethicone

Imidazolidinyl Urea

Benzophenone-3

Cetearyl Dimethicone Crosspolymer

Sodium Chloride

Hydrolyzed Extensin

Phospholipids

Parfum

Phenoxyethanol

Betaine

Collagen

INDICATIONS AND USAGE

Apply over your body daily
in the morning andbefore bed.

DOSAGE AND ADMINISTRATION

Apply over your body daily in the morning and before bed.

PURPOSE

Moisturizing

WARNINGS

For external use only.

Stop use and ask a doctor if rash occurs.

When using this product keep out of eyes. Rinse with water to remove.

Keep out of reach of children. If swallowed, get medical help or contact a Poison Control Center right away.